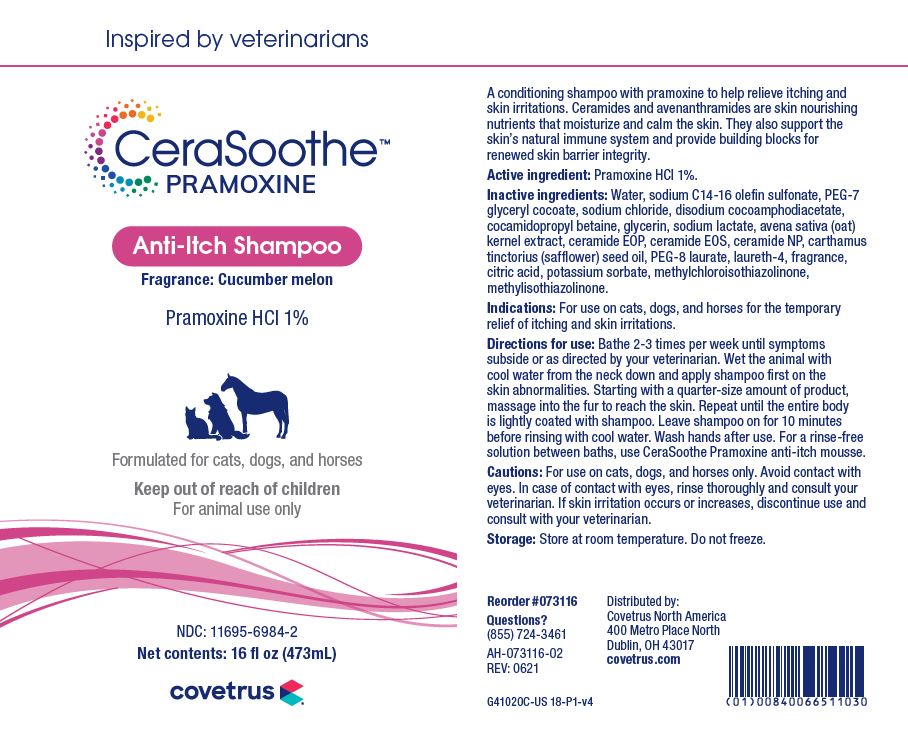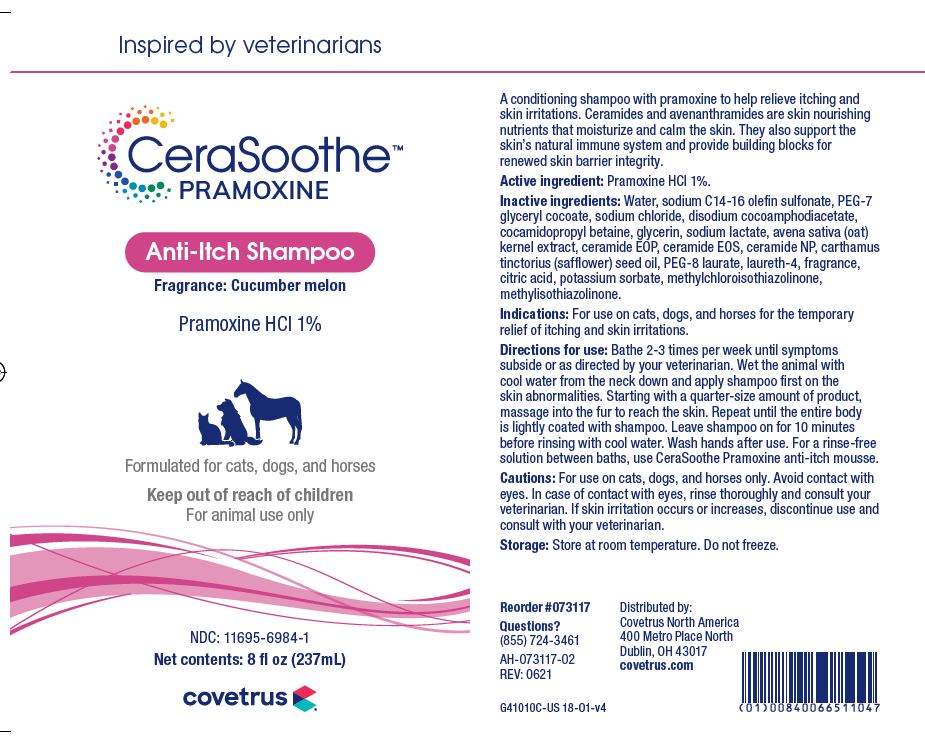 DRUG LABEL: CeraSoothe
NDC: 11695-6984 | Form: SHAMPOO
Manufacturer: BUTLER ANIMAL HEALTH SUPPLY, LLC DBA COVETRUS NORTH AMERICA
Category: animal | Type: OTC ANIMAL DRUG LABEL
Date: 20220524

ACTIVE INGREDIENTS: PRAMOXINE HYDROCHLORIDE 10 mg/1 mL
INACTIVE INGREDIENTS: WATER; SODIUM C14-16 OLEFIN SULFONATE; PEG-7 GLYCERYL COCOATE; SODIUM CHLORIDE; DISODIUM COCOAMPHODIACETATE; COCAMIDOPROPYL BETAINE; GLYCERIN; SODIUM LACTATE; AVENANTHRAMIDES; CERAMIDE 1; CERAMIDE EOS; CERAMIDE NP; SAFFLOWER OIL; PEG-8 LAURATE; LAURETH-4; CITRIC ACID MONOHYDRATE; POTASSIUM SORBATE; METHYLCHLOROISOTHIAZOLINONE; METHYLISOTHIAZOLINONE

DESCRIPTION

CeraSoothe

PRAMOXINE

Anti-Itch Shampoo

Fragrance: Cucumber melon

Pramoxine HCl 1%

Formulated for cats, dogs and horses

A conditioning shampoo with pramoxine to help relieve itching and skin irritations. Ceramides and avenanthramides are skin nourishing nutrients that moisturize and calm the skin. They also support the skin's natural immune system and provide building blocks for renewed skin barrier integrity.

Active ingredient: Pramoxine HCI 1%.

Inactive ingredients: Water, sodium C14-16 olefin sulfonate, PEG-7 glyceryl cocoate, sodium chloride, disodium cocoamphodiacetate, cocamidopropyl betaine, glycerin, sodium lactate, avena sativa (oat) kernal extract, ceramide EOP, ceramide EOS, ceramide NP, carthamus tinctorius (safflower) seed oil, PEG-8, laurate, laureth-4, fragrance, citric acid, potassium sorbate, methylchloroisothiazolinone, methylisothiazolinone.

INDICATIONS AND USAGE

Indications: For use on cats, dogs and horses for the temporary relief of itching and skin irritations.

Directions for use: Bathe 2-3 times per week until symptoms subside or as directed by your veterinarian. Wet the animal with cool water from the neck down and apply shampoo first on the skin abnormalities. Starting with a quarter-size amount of product, massage into the fur to reach the skin. Repeat until the entire body is lightly coated with shampoo. Leave shampoo on for 10 minutes before rinsing with cool water. Wash hands after use. For a rinse-free solution between baths, use Ceraven Pramoxine anti-itch mousse.

WARNINGS AND PRECAUTIONS

Cautions: For external use on cats, dogs and horses only. Avoid contact with eyes. In case of contact with eyes, rinse thoroughly and consult your veterinarian. If skin irritation occurs or increases, discontinue use and consult with your veterinarian.

STORAGE AND HANDLING

STORAGE CONDITIONS: Store at room temperature. Do not freeze.

Distributed by:

Covetrus North America

400 Metro Place North

Dublin, OH 43017

covetrus.com

QUESTIONS?

(855) 724-3461

PRINCIPAL DISPLAY PANEL - 8 OUNCE (237 mL) Bottle

Inspired by veterinarians

CeraSoothe

PRAMOXINE

Anti-itch Shampoo

Fragrance: Cucumber melon

Pramoxine HCl 1%

Formulated for cats, dogs and horses

Keep out of reach of children

For animal use only

NDC: 11695-6984-1

Net contents: 8 fl oz (237 mL)

PRINCIPAL DISPLAY PANEL - 16 OUNCE (473 mL) Bottle

Inspired by veterinarians

CeraSoothe

PRAMOXINE

Anti-itch Shampoo

Fragrance: Cucumber melon

Pramoxine HCl 1%

Formulated for cats, dogs and horses

Keep out of reach of children

For animal use only

NDC: 11695-6984-2

Net contents: 16 fl oz (473 mL)